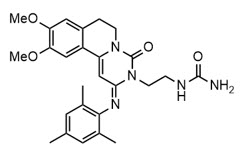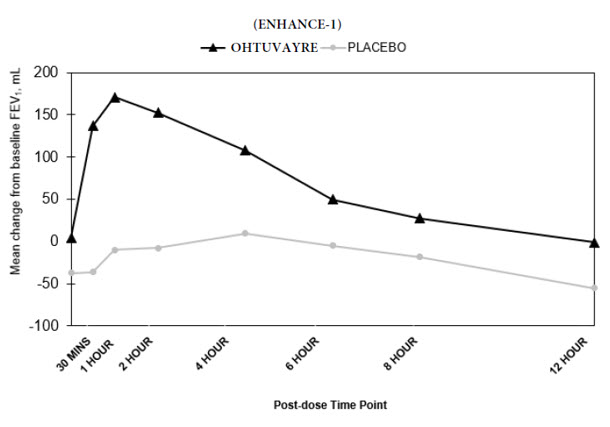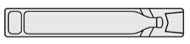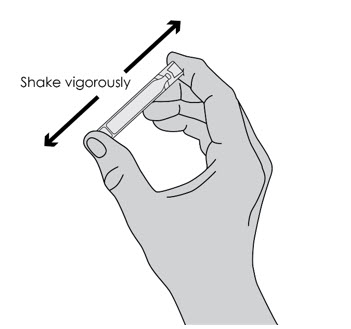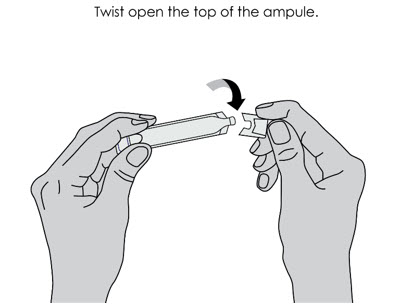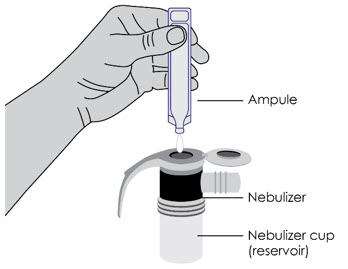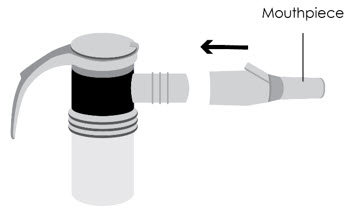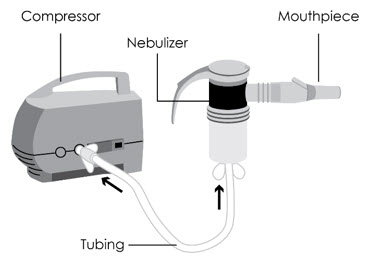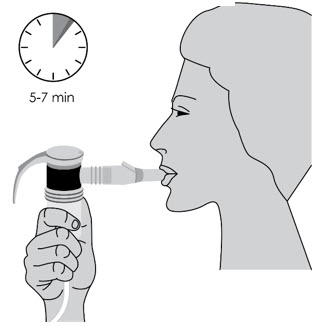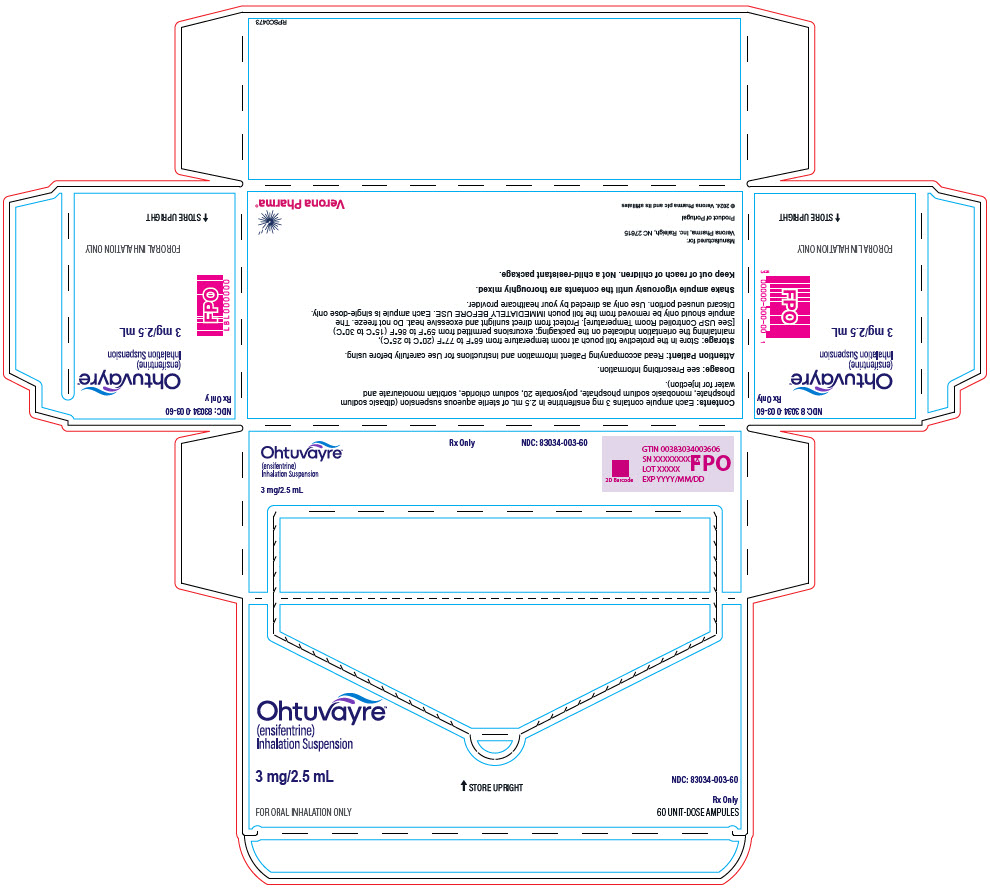 DRUG LABEL: Ohtuvayre
NDC: 83034-003 | Form: SUSPENSION
Manufacturer: Verona Pharma, Inc.
Category: prescription | Type: HUMAN PRESCRIPTION DRUG LABEL
Date: 20250731

ACTIVE INGREDIENTS: ensifentrine 3 mg/2.5 mL
INACTIVE INGREDIENTS: sodium chloride; SODIUM PHOSPHATE, DIBASIC, DIHYDRATE; SODIUM PHOSPHATE, MONOBASIC, DIHYDRATE; polysorbate 20; sorbitan monolaurate; water

HIGHLIGHTS OF PRESCRIBING INFORMATION

These highlights do not include all the information needed to use OHTUVAYRE™ safely and effectively. See full prescribing information for OHTUVAYRE.
OHTUVAYRE (ensifentrine) inhalation suspension, for oral inhalation use
Initial U.S. Approval: 2024

1 INDICATIONS AND USAGE

OHTUVAYRE is a phosphodiesterase 3 (PDE3) inhibitor and phosphodiesterase 4 (PDE4) inhibitor indicated for the maintenance treatment of chronic obstructive pulmonary disease (COPD) in adult patients. (1)

2 DOSAGE AND ADMINISTRATION

Recommended Dosage: 3 mg (one ampule) twice daily administered by oral inhalation using a standard jet nebulizer with a mouthpiece. (2)

- See full prescribing information for administration instructions. (2)

3 DOSAGE FORMS AND STRENGTHS

Inhalation suspension: 3 mg/2.5 mL aqueous suspension in unit-dose ampules. (3)

4 CONTRAINDICATIONS

OHTUVAYRE is contraindicated in patients with hypersensitivity to ensifentrine or any component of this product. (4)

5 WARNINGS AND PRECAUTIONS

- Should not use OHTUVAYRE to treat acute symptoms of bronchospasm. (5.1)
- If paradoxical bronchospasm occurs, discontinue OHTUVAYRE and institute alternative therapy. (5.2)
- An increase in psychiatric adverse reactions, including suicidality, were reported with use of OHTUVAYRE. Carefully weigh the risks and benefits of treatment with OHTUVAYRE in patients with a history of depression and/or suicidal thoughts or behavior. (5.3)

6 ADVERSE REACTIONS

Most common adverse reactions (incidence greater and equal to 1% and more common than placebo) include back pain, hypertension, urinary tract infection, and diarrhea. (6.1)

To report SUSPECTED ADVERSE REACTIONS, contact Verona Pharma at 888-672-0371 or FDA at 1-800-FDA-1088 or www.fda.gov/medwatch.

8 USE IN SPECIFIC POPULATIONS

Hepatic impairment: Ensifentrine exposure increases in patients with hepatic impairment. Use with caution. (8.6, 12.3)

FULL PRESCRIBING INFORMATION

1 INDICATIONS AND USAGE

OHTUVAYRE is indicated for the maintenance treatment of chronic obstructive pulmonary disease (COPD) in adult patients.

2 DOSAGE AND ADMINISTRATION

The recommended dosage of OHTUVAYRE is 3 mg (one unit-dose ampule) twice daily, once in the morning and once in the evening, administered by oral inhalation using a standard jet nebulizer with a mouthpiece.

Administration Instructions

- Remove OHTUVAYRE unit-dose ampule from foil pouch only immediately before use. For pouches of 5 ampules, remove one ampule and place the remaining ampules back into the pouch until next use. Once the foil pouch is opened, discard ampules if not used within 14 days.
- Shake OHTUVAYRE ampule vigorously.
- Squeeze and completely empty contents of the ampule into the nebulizer cup for administration of OHTUVAYRE by oral inhalation. Discard ampule with any residual content.
- Administer OHTUVAYRE by oral inhalation using a standard jet nebulizer equipped with a mouthpiece, connected to an air compressor [see Instructions for Use].

Drug Compatibility

Compatibility of OHTUVAYRE mixed with other drugs has not been established. OHTUVAYRE should not be physically mixed with other drugs or added to solutions containing other drugs.

3 DOSAGE FORMS AND STRENGTHS

Inhalation suspension: 3 mg/2.5 mL (1.2 mg/mL) of sterile, yellow to pale yellow, aqueous suspension in low-density polyethylene unit-dose ampules.

4 CONTRAINDICATIONS

OHTUVAYRE is contraindicated in patients with hypersensitivity to ensifentrine or any component of this product.

5 WARNINGS AND PRECAUTIONS

5.1 Acute Episodes of Bronchospasm

OHTUVAYRE should not be used for the relief of acute symptoms, i.e., as rescue therapy for the treatment of acute episodes of bronchospasm. OHTUVAYRE has not been studied in the relief of acute symptoms and extra doses of OHTUVAYRE should not be used for that purpose. The safety and effectiveness of OHTUVAYRE for relief of acute symptoms have not been established. Acute symptoms should be treated with an inhaled, short-acting bronchodilator.

5.2 Paradoxical Bronchospasm

As with other inhaled medicines, OHTUVAYRE may produce paradoxical bronchospasm, which may be life threatening. If paradoxical bronchospasm occurs following dosing with OHTUVAYRE, it should be treated immediately with an inhaled, short-acting bronchodilator. OHTUVAYRE should be discontinued immediately and alternative therapy should be instituted.

5.3 Psychiatric Events Including Suicidality

Treatment with OHTUVAYRE is associated with an increase in psychiatric adverse reactions. Psychiatric events including suicide-related adverse reactions were reported in clinical studies in patients who received OHTUVAYRE. One patient who received OHTUVAYRE in the pooled 24-week safety population [see Adverse Reactions (6.1)] experienced a suicide-related adverse reaction (suicide attempt), and in another controlled study, one patient who received ensifentrine experienced a suicide-related adverse reaction (suicide). Additionally, the most commonly reported psychiatric adverse reactions in the pooled 24-week safety population were insomnia (6 patients [0.6%] OHTUVAYRE 3 mg; 2 patients [0.3%] placebo), and anxiety (2 patients [0.2%] OHTUVAYRE 3 mg; 1 patient [0.2%] placebo). Depression-related reactions including depression, major depression, and adjustment disorder with depressed mood occurred in 4 patients [0.4%] receiving OHTUVAYRE and no patients receiving placebo.

Before initiating treatment with OHTUVAYRE, healthcare providers should carefully weigh the risk and benefits of treatment with OHTUVAYRE in patients with a history of depression and/or suicidal thoughts or behavior. Healthcare providers should carefully evaluate the risks and benefits of continuing treatment with OHTUVAYRE if such events occur.

6 ADVERSE REACTIONS

The following clinically significant adverse reactions are described elsewhere in the labeling:

- Paradoxical Bronchospasm [see Warnings and Precautions (5.2)]
- Psychiatric Events Including Suicidality [see Warnings and Precautions (5.3)]

6.1 Clinical Trials Experience

Because clinical trials are conducted under widely varying conditions, adverse reaction rates observed in the clinical trials of a drug cannot be directly compared to rates in the clinical trials of another drug and may not reflect the rates observed in practice.

The safety of OHTUVAYRE was based on the pooled safety population from two randomized, double-blind, placebo-controlled trials (ENHANCE-1 and ENHANCE-2) for 24 weeks, and a 48-week cohort that assessed safety in ENHANCE-1. In these trials, a total of 975 patients received 3 mg of OHTUVAYRE twice daily administered by oral inhalation using a standard jet nebulizer [see Clinical Studies (14)]. The safety population included all patients who were randomized and received at least one dose of OHTUVAYRE or placebo.

Adverse reactions that occurred at an incidence greater than or equal to 1% in OHTUVAYRE and were more common than placebo in the pooled population are provided in Table 1.

The proportion of patients who discontinued treatment due to adverse reactions was 7.6% for the OHTUVAYRE-treated patients and 8.2% for placebo-treated patients.

Table 1. Adverse Reactions with OHTUVAYRE with incidence ≥ 1% and More Common than Placebo in Patients with COPD in the Pooled 24-Week Safety Population (ENHANCE-1 and ENHANCE-2)
Adverse Reaction | OHTUVAYRE N=975 n (%) | Placebo N=574 n (%)
Back pain | 18 (1.8%) | 6 (1.0%)
Hypertension | 17 (1.7%) | 5 (0.9%)
Urinary tract infection | 13 (1.3%) | 6 (1.0%)
Diarrhea | 10 (1.0%) | 4 (0.7%)

Adverse Reactions in the 48-Week Cohort

In the 48-week cohort of ENHANCE-1, 369 patients were enrolled to be treated with 3 mg OHTUVAYRE (N=280) or placebo (N=89) twice daily for 48 weeks [see Clinical Studies (14)]. The adverse reactions reported in the 48-week cohort were consistent with those observed in the pooled 24-week safety population.

8 USE IN SPECIFIC POPULATIONS

8.1 Pregnancy

Risk Summary

There are no available data on OHTUVAYRE use in pregnant women to evaluate for a drug-associated risk of major birth defects, miscarriage or other adverse maternal or fetal outcomes. In animal reproduction studies, administration of inhaled ensifentrine at exposures 30 times the exposure at the maximum recommended human daily inhalation dose (MRHDID) to male rats for 10 weeks prior to mating with untreated females produced increased pre- and post- implantation loss, and decreased live embryos in untreated female rats. No adverse developmental effects were observed with inhalation administration of ensifentrine to pregnant rats and rabbits during organogenesis at maternal exposures up to 79 and 9 times the exposure at MRHDID, respectively. No adverse developmental effects were observed after inhaled administration of ensifentrine to pregnant rats from the period of organogenesis through lactation at exposures up to approximately 79 times the MRHDID. (see Data).

The estimated background risk of major birth defects and miscarriage for the indicated population is unknown. All pregnancies have a background risk of birth defect, loss, or other adverse outcomes. In the U.S. general population, the estimated background risk of major birth defects and miscarriage in clinically recognized pregnancies is 2% to 4% and 15% to 20%, respectively.

Data

Animal Data

In a male fertility study, ensifentrine was administered to male rats at inhalation doses of 2, 6, and 16 mg/kg/day (4, 13, and 30 times the exposure at the MRHDID) for 10 weeks prior to mating to untreated females. Adverse effects at 16 mg/kg/day (30 times the exposure at the MRHDID) on reproductive performance included increased pre- and post- implantation loss, and decreased live embryos per litter in untreated females. No developmental toxicity was observed in rats at 6 mg/kg/day (13 times the exposure at the MRHDID).

In an embryo-fetal development study, pregnant rats were administered ensifentrine at inhalation doses of up to 15 mg/kg/day (79 times the exposure at the MRHDID) during the period of organogenesis from gestation Days 6 to 17. Ensifentrine did not cause adverse effects to the fetus at exposures up to 79 times the MRHDID (on an AUC basis at a maternal inhalation dose of 15 mg/kg/day).

In an embryo-fetal development study, pregnant rabbits were administered ensifentrine at inhalation doses of up to 12 mg/kg/day (9 times the exposure at the MRHDID) during the period of organogenesis from gestation Days 6 to 19. Ensifentrine did not cause adverse effects to the fetus at maternal exposures up to 9 times the MRHDID.

In a pre- and post-natal development (PPND) study, pregnant rats were administered ensifentrine at inhalation doses of up to 19 mg/kg/day (approximately 79 times the exposure at the MRHDID) from gestation day 6 to lactation/post-partum day 24. No adverse effects were observed in the offspring exposed daily from birth (in utero) through lactation at maternal pulmonary deposited doses up to approximately 79 times the MRHDID.

8.2 Lactation

Risk Summary

There are no data on the presence of ensifentrine in human milk, the effects on the breastfed child, or the effects on milk production. There are no data from animal studies on the presence of ensifentrine in milk.

The developmental and health benefits of breastfeeding should be considered along with the mother's clinical need for OHTUVAYRE and any potential adverse effects on the breastfed child from OHTUVAYRE or from the underlying maternal condition.

8.4 Pediatric Use

The safety and effectiveness of OHTUVAYRE have not been established in pediatric patients.

8.5 Geriatric Use

There were 852 patients aged 65 years and older in ENHANCE-1 and ENHANCE-2 for COPD [see CLINICAL STUDIES (14)]. Of the total number of patients randomized to receive OHTUVAYRE in these trials, 534 (55%) were 65 years of age and older, while 84 (9%) were 75 years and older. No overall differences in safety or effectiveness of OHTUVAYRE have been observed between these patients and younger adult patients, but greater sensitivity of some older individuals cannot be ruled out.

8.6 Hepatic Impairment

Ensifentrine systemic exposure increased by 2.3-fold in subjects with moderate or severe hepatic impairment compared with healthy subjects [see Clinical Pharmacology (12.3)]. Use OHTUVAYRE with caution in patients with hepatic impairment.

8.7 Renal Impairment

No dosage adjustment in patients with mild or moderate renal impairment is required. Patients with severe renal impairment have not been evaluated [see Clinical Pharmacology (12.3)].

10 OVERDOSAGE

An overdosage of OHTUVAYRE may lead to signs and symptoms such as headache, tachycardia, and palpitations. Treatment of overdosage consists of temporary interruption of OHTUVAYRE along with appropriate symptomatic and/or supportive therapy.

11 DESCRIPTION

OHTUVAYRE (ensifentrine) is a sterile, yellow to pale yellow aqueous inhalation suspension of ensifentrine for oral inhalation. Ensifentrine, the active component of OHTUVAYRE, is an inhibitor of phosphodiesterases 3 and 4 (PDE3 and PDE4). The chemical name for ensifentrine is N-(2-{(2E)-9,10-dimethoxy-4-oxo-2-[(2,4,6-trimethylphenyl)imino]-6,7-dihydro-2H-pyrimido[6,1-a]isoquinolin-3(4H)-yl}ethyl)urea; its structural formula is:

Ensifentrine has a molecular weight of 477.56 and its empirical formula is C26H31N5O4. Ensifentrine is a yellow to pale yellow crystalline powder which is practically insoluble in water.

OHTUVAYRE is supplied as 2.5 mL of sterile ensifentrine (1.2 mg/mL) suspension packaged in a unit-dose low-density polyethylene ampule overwrapped in a sealed foil pouch. Each unit-dose ampule contains 3 mg ensifentrine suspended in a pH 6.7 aqueous solution containing dibasic sodium phosphate, monobasic sodium phosphate, polysorbate 20, sodium chloride, sorbitan monolaurate and water for injection.

The ampule containing OHTUVAYRE should be shaken vigorously to ensure complete resuspension of the active ingredient immediately prior to administration by nebulization. Like all other nebulized treatments, the amount delivered to the lungs will depend on patient factors, the nebulization system used, and compressor performance.

Using the PARI LC Sprint® jet nebulizer attached to a PARI Vios Pro® compressor under in vitro conditions, the mean delivered dose from the mouthpiece was approximately 933 micrograms (31% of label claim) at a mean flow rate of approximately 5 liters per minute. The mean nebulization time was approximately 7 minutes. The mass median aerodynamic diameter (MMAD) of the nebulized particles/droplets using the PARI LC Sprint® jet nebulizer attached to a PARI Vios Pro® compressor (flow rate approximately 15 L per minute, nebulization time approximately 10 minutes) is 5.82 microns (geometric standard deviation = 1.97) with a typical fine particle dose (mass of aerosolized drug < 5 microns) of approximately 614 micrograms, as determined using the Next Generation Impactor (NGI) method, based on USP <601>. OHTUVAYRE should only be administered via a standard jet nebulizer connected to an air compressor with an adequate airflow and equipped with a mouthpiece.

12 CLINICAL PHARMACOLOGY

12.1 Mechanism of Action

Ensifentrine is a small molecule that is an inhibitor of the PDE3 and PDE4 enzymes. PDE3 primarily hydrolyzes the second-messenger molecule cyclic adenosine monophosphate (cAMP) but is also capable of hydrolyzing cyclic guanosine monophosphate (cGMP). PDE4 hydrolyzes cAMP only. Inhibition of PDE3 and PDE4 results in accumulation of intracellular levels of cAMP and/or cGMP, resulting in various downstream signalling effects.

12.2 Pharmacodynamics

Cardiac Electrophysiology

QTc interval prolongation was studied in a randomized, double-blind, placebo- and positive-controlled, 4-period crossover study in 32 healthy subjects. At 3 times the maximum recommended dose, clinically significant QTc interval prolongation was not observed.

12.3 Pharmacokinetics

Exposure to ensifentrine increased approximately 1.4-fold greater than dose proportional following a dose 3 times the recommended dosage. Steady-state was attained by Day 3 following twice-daily dosing. Population pharmacokinetic analysis predicts accumulation of ensifentrine of 1.3 and 1.4-fold for Cmax and AUC in healthy subjects and 1.4 and 1.5-fold for Cmax and AUC in subjects with COPD. Population pharmacokinetic analysis indicates that relative bioavailability in subjects with COPD is approximately 35% lower when compared to healthy subjects. Exposure to ensifentrine was associated with high inter-subject variability.

Absorption

Following inhaled administration of OHTUVAYRE in healthy subjects and subjects with COPD, ensifentrine Cmax was attained around 0.6 to 1.5 hours after dosing.

A randomized, 2-period, cross-over study assessing systemic exposure following inhalation of 2 times the recommended dose of ensifentrine with and without charcoal block demonstrated that the majority of an inhaled dose (approximately 90%) is delivered to the lung from which it is absorbed.

Distribution

Apparent central and peripheral volume of distribution for ensifentrine in healthy subjects were 2700 L and 1820 L, respectively, as estimated in population PK analysis. In patients with COPD, apparent central and peripheral volumes were estimated as 8150 L and 5490 L, respectively.

In vitro plasma protein binding of ensifentrine is approximately 90%.

Elimination

Following twice-daily administration for 6 days, terminal elimination half-life ranged from 10.6 to 12.6 hours in healthy subjects and subjects with COPD (1.5 mg to 12 mg twice daily).

Metabolism

Following administration of a single nebulized dose, 8 times the recommended dose of ensifentrine, unchanged ensifentrine was identified as the major drug-related component in human plasma, accounting for 96 and 99% of the drug-related material identified in Tmax and time-normalized (0-24 h) plasma samples, respectively.

The primary metabolic routes for ensifentrine are oxidative (hydroxylation, O-demethylation) followed by conjugation (e.g., glucuronidation).

In vitro results indicate that, at physiologically relevant concentrations, ensifentrine was predominantly metabolized by CYP2C9 and to a lesser extent by CYP2D6.

Excretion

The majority of ensifentrine is excreted in feces. After a 3 mg nebulized dose, urinary elimination of unchanged ensifentrine was negligible (<0.3% of the dose).

Specific Populations

Population pharmacokinetic analysis showed no evidence of a clinically significant effect of demographic covariates such as age (18 to 80 years), sex (56% male), ethnicity (Hispanic, Non-Hispanic), race (white, black) and weight (42 to 180 kg) on ensifentrine pharmacokinetics.

Patients with Renal Impairment

A dedicated study with OHTUVAYRE evaluating the effect of renal impairment on the pharmacokinetics of ensifentrine was not conducted.

The effect of renal impairment on the exposure to ensifentrine for up to 24 weeks was evaluated in a population pharmacokinetic analysis. Estimated glomerular filtration rate (eGFR) varied from 25.5 to 191 mL/min representing a range of moderate to no renal impairment. While continuous covariates of renal function did not show a significant correlation with ensifentrine exposure, categorical characterization of renal function indicated a 25% mean reduction in the apparent clearance in subjects with moderate renal impairment. The pharmacokinetics of ensifentrine in severe renal impairment (creatine clearance <30 mL/min) or subjects with end-stage renal disease have not been evaluated.

Patients with Hepatic Impairment

The pharmacokinetics of ensifentrine were evaluated in subjects with moderate (Child-Pugh Class B) (N=10) to severe (Child-Pugh Class C) (N=2) hepatic impairment. Ensifentrine Cmax and AUCinf were approximately 2.3-fold and 2.2-fold higher in subjects with moderate hepatic impairment compared with healthy controls. Ensifentrine Cmax and AUCinf were approximately 1.2-fold and 2.3-fold higher in subjects with severe hepatic impairment compared with healthy controls (N=7).

Population PK analysis did not identify markers of liver function (ALT, AST, bilirubin, and ALP) as a significant covariate for exposure of ensifentrine.

Drug Interaction Studies

Effect of Other Drugs on OHTUVAYRE

Clinical Studies

Ensifentrine and Cytochrome P450: Ensifentrine Cmax and AUC0-inf were 1.4-fold and 1.6-fold higher; respectively, when a 3 mg single dose of OHTUVAYRE was concomitantly administered with CYP2C9 inhibitor fluconazole (200 mg twice daily).

In Vitro Studies

Ensifentrine and Efflux Transporters: Ensifentrine is not a substrate of the efflux transporter P-glycoprotein (P-gp). Ensifentrine is a substrate of breast cancer resistance protein (BCRP).

Ensifentrine and Uptake Transporters: Ensifentrine is not a substrate of the uptake transporters OATP1B1 or OATP1B3.

Effect of OHTUVAYRE on Other Drugs

In Vitro Studies

Ensifentrine and Cytochrome P450: At therapeutically relevant concentrations, ensifentrine does not inhibit CYP1A2, CYP2B6, CYP2C8, CYP2C9, CYP2C19, CYP2D6, or CYP3A4.

Ensifentrine and Efflux Transporters: At therapeutically relevant concentrations, ensifentrine is not an inhibitor of either BCRP or P-gp.

Ensifentrine and Uptake Transporters: Ensifentrine does not inhibit the transporters, OATP1B1, OATP1B3, OAT1, OAT3, OCT2, MATE1 or MATE2-K, at therapeutically relevant concentrations.

13 NONCLINICAL TOXICOLOGY

13.1 Carcinogenesis, Mutagenesis, Impairment of Fertility

A two-year inhalation study in Han Wistar rats and a 6-month oral study in Tg.rasH2 transgenic mice were conducted to assess the carcinogenic potential of ensifentrine. No evidence of tumorigenicity was observed in male and female rats at an exposure approximately 40 times the MRHDID. No evidence of tumorigenicity was observed in male and female Tg.rasH2 mice at oral doses up to 80 mg/kg/day, the highest dose tested.

Ensifentrine was negative for genotoxicity in the following assays: in vitro Ames test for bacterial gene mutation, in vivo comet test with rats, or in vivo micronucleus assay with mice.

In a male fertility study, ensifentrine was administrated to male rats at inhalation doses of 2, 6, and 16 mg/kg/day (4, 13, and 30 times the exposure at the MRHDID) for 10 weeks prior to mating to untreated females. Male rats had decreased sperm motility and increased abnormal sperm morphology at an inhalation dose of 16 mg/kg/day (approximately 30 times the exposure at the MRHDID). Decreased sperm counts in the testis were observed at all doses. Atrophy/degeneration in the testis and intraluminal germ cell debris in the epididymis were observed at doses of 6 (13 times the exposure at the MRHDID) and 16 mg/kg/day (30 times the exposure at the MRHDID). Additional adverse effects at 16 mg/kg/day on reproductive performance included decreased mating index and decreased fertility index. The sperm counts, sperm motility, and sperm morphology were reversible at the end of a 4-week treatment-free period. Atrophy/degeneration in the testis and intraluminal germ cell debris in the epididymis were not present at the end of a 4-week treatment-free period. In a female fertility study, ensifentrine was administrated to female rats at inhalation doses of up to 18 mg/kg/day from two weeks prior to mating to 7 days after mating. Ensifentrine had no effect on female fertility and reproductive performance indices up to 18 mg/kg/day (31 times the exposure at the MRHDID).

14 CLINICAL STUDIES

The efficacy of OHTUVAYRE was evaluated in two 24-week randomized, double-blind, placebo-controlled, parallel-group clinical trials (ENHANCE-1 [NCT04535986] and ENHANCE-2 [NCT04542057]). The two trials enrolled a total of 1553 adults with moderate to severe COPD.

ENHANCE-1 enrolled a total of 763 patients randomized 5:3 to receive 3 mg of OHTUVAYRE administered by oral inhalation via standard jet nebulizer such as PARI LC Sprint® [see Description (11)], or placebo. Patients in ENHANCE-1 had a mean age of 65 years (range: 41 to 80 years), were 58% male, 90% White, 3% Black/African American, 3% Asian, 0.1% Other race, and 3% Hispanic or Latino ethnicity. Patients had a mean smoking history of 41 pack-years and 57% were current smokers, and 25% of patients reported exacerbations of COPD within the 15 months prior to the study. At screening, the mean post-bronchodilator percent predicted FEV1 was 52% (range: 27% to 85%), and the mean post-bronchodilator FEV1/FVC ratio was 0.52 (range: 0.22 to 0.71). In addition, 68% of patients were taking concurrent therapy: 30% taking concurrent LAMA, 18% taking concurrent LABA, and 20% taking concurrent LABA/ICS therapy throughout the trial.

ENHANCE-2 enrolled a total of 790 patients randomized 5:3 to receive 3 mg of OHTUVAYRE twice daily administered by oral inhalation via a standard jet nebulizer such as PARI LC Sprint® [see Description (11)] or placebo. Patients in ENHANCE-2 had a mean age of 65 years (range: 40 to 80 years), were 52% female, 95% White, 4% Black/African American, 0.3% Asian, 0.5% Other race, and 5% Hispanic or Latino ethnicity. Patients had a mean smoking history of 42 pack-years and 55% were current smokers, and 21% of patients reported exacerbations of COPD within the 15 months prior to the study. At screening, the mean post-bronchodilator percent predicted FEV1 was 51% (range: 23% to 81%), and the mean post-bronchodilator FEV1/FVC ratio was 0.52 (range: 0.24 to 0.71). In addition, 55% of patients were taking concurrent therapy: 33% taking concurrent LAMA, 7% taking concurrent LABA, and 15% taking concurrent LABA/ICS therapy throughout the trial.

The primary endpoint for ENHANCE-1 and ENHANCE-2 was the change from baseline in FEV1 AUC0-12h post dose at Week 12. In both trials, OHTUVAYRE demonstrated a statistically significant improvement in FEV1 AUC0-12h compared to placebo. Refer to Table 2 for the primary endpoint results.

Table 2. Least Squares (LS) Mean Change from Baseline in FEV1 AUC0-12h (mL) at Week 12 in ENHANCE-1 and ENHANCE-2
 | ENHANCE-1 |  | ENHANCE-2
 | OHTUVAYRE (N=479) | Placebo (N=284) | OHTUVAYRE (N=499) | Placebo (N=291)
n | 477 | 282 | 498 | 291
LS Mean (95% CI) | 61 (25, 97) | -26 (-64, 13) | 48 (30, 66) | -46 (-70, -22)
LS Mean Difference from Placebo (95% CI) | 87 (55, 118) | - | 94 (65, 124) | -
p-value | <0.0001 | - | <0.0001 | -
CI, confidence interval; LS, least squares; N= number of all enrolled patients; n = number of patients who received at least one dose of study drug and had non-missing baseline FEV1 value.

In ENHANCE-1 and ENHANCE-2, serial spirometry was performed over 12 hours in all patients at baseline and Week 12. Serial spirometry data for ENHANCE-1 at Week 12 are shown in Figure 1.

Figure 1. Mean FEV1 (mL) Change from Baseline over 12 hours at Week 12 (ENHANCE-1)

Trough FEV1 was defined as the last FEV1 value collected prior to the morning dose. The mean morning trough FEV1 improvement at Week 12 relative to placebo was 35 mL (95% CI: 14, 68) and 49 mL (95% CI: 19, 80) in ENHANCE-1 and ENHANCE-2, respectively, which was statistically significant in ENHANCE-1, and not statistically significant in ENHANCE-2 due to failure higher in the testing hierarchy.

Health-Related Quality of Life

The St. George's Respiratory Questionnaire (SGRQ) was assessed in ENHANCE-1 and ENHANCE-2. In ENHANCE-1, the SGRQ responder rate (defined as an improvement in score of 4 or more as threshold) for OHTUVAYRE at Week 24 was 58.2% compared to 45.9% for placebo [Odds Ratio: 1.49; 95% CI: 1.07, 2.07]. In ENHANCE-2, the SGRQ responder rate for OHTUVAYRE at Week 24 was 45.4% compared to 50.3% for placebo [Odds Ratio: 0.92; 95% CI: 0.66, 1.29].

16 HOW SUPPLIED/STORAGE AND HANDLING

OHTUVAYRE (ensifentrine) 3 mg/2.5 mL inhalation suspension is a sterile aqueous suspension in a unit-dose low-density polyethylene ampule. OHTUVAYRE is supplied as:

- Carton of 60: 60 pouches of 1 unit-dose ampule (NDC 83034-003-60)
- Carton of 60: 12 pouches of 5 unit-dose ampules (NDC 83034-003-65)

Ampules are overwrapped in a sealed foil pouch. The ampule containing OHTUVAYRE should be shaken vigorously to ensure complete resuspension of the active ingredient immediately prior to use. The used ampule and any residual content should be discarded after use.

STORAGE AND HANDLING

Store OHTUVAYRE in the protective foil pouch. Only remove an ampule from foil pouch immediately before use. For pouches of 5 ampules, remove one ampule and place the remaining ampules back into the foil pouch until next use. Once the foil pouch is opened, discard ampules if not used within 14 days. Store at controlled room temperature (68°F to 77°F [20°C to 25°C], excursions permitted from 59ºF to 86ºF [15ºC to 30ºC]) [See USP Controlled Room Temperature], maintaining the orientation indicated on the carton. Protect from direct sunlight and excessive heat. Do not freeze.

17 PATIENT COUNSELING INFORMATION

Advise the patient to read the FDA-approved patient labeling (Patient Information and Instructions for Use).

Not for Treatment of Acute Symptoms of Bronchospasm

Inform patients that OHTUVAYRE is not meant to relieve acute symptoms of COPD and extra doses should not be used for that purpose. Advise patients to treat acute symptoms with an inhaled, short-acting beta2-agonist such as albuterol [see Warnings and Precautions (5.1)]. Provide patients with such medicine and instruct them in how it should be used.

Instruct patients to seek medical attention immediately if they experience any of the following:

- Decreasing effectiveness of inhaled, short-acting beta2-agonists
- Need for more inhalations than usual of inhaled, short-acting beta2-agonists
- Significant decrease in lung function as outlined by the health care provider

Paradoxical Bronchospasm

As with other inhaled medicines, OHTUVAYRE can cause paradoxical bronchospasm. If paradoxical bronchospasm occurs, instruct patients to discontinue OHTUVAYRE [see Warnings and Precautions (5.2)].

Psychiatric Events Including Suicidality

Advise patients, caregivers, and families to be alert for the emergence or worsening of insomnia, anxiety, depression, suicidal thoughts or other mood changes, and if such changes occur to contact their healthcare provider so that the risks and benefits of continuing treatment with OHTUVAYRE may be considered [see Warnings and Precautions (5.3)].

Administration Instructions

Instruct patients that OHTUVAYRE should only be administered via a standard jet nebulizer [see Instructions for Use]. Patients should be instructed not to inject or swallow OHTUVAYRE. Patients should be instructed not to mix other medications with OHTUVAYRE in a nebulizer.

Inform patients to use the contents of one ampule of OHTUVAYRE orally inhaled twice daily, once in the morning and once in the evening. Instruct patients to vigorously shake OHTUVAYRE to ensure complete resuspension of the active ingredient immediately prior to use [see Dosage and Administration (2)].

Manufactured for:
Verona Pharma, Inc.
8529 Six Forks Road, Suite #400
Raleigh, NC 27615

©2025. Verona Pharma plc and its affiliates
Verona Pharma, OHTUVAYRE and the Verona Pharma and OHTUVAYRE logos are all trademarks of Verona Pharma plc
PI002

PATIENT INFORMATION
OHTUVAYRE (OH-too-vare)
(ensifentrine)
inhalation suspension, for oral inhalation

Important: For oral inhalation only. Do not swallow or inject OHTUVAYRE.

What is OHTUVAYRE?

- OHTUVAYRE is a prescription medicine used to treat chronic obstructive pulmonary disease (COPD) in adults. COPD is a chronic (long-term) lung disease that includes chronic bronchitis, emphysema, or both.
- OHTUVAYRE is an inhibitor of phosphodiesterases 3 and 4 (PDE3 and PDE4).
- Decreasing PDE3 activity helps the muscles around the airways in your lungs stay relaxed to prevent symptoms such as wheezing, coughing, chest tightness, and shortness of breath, which can happen when muscles around the airway tighten, making it hard to breathe. Decreasing PDE4 activity helps to decrease inflammation in the lungs. Inflammation in the lungs can lead to breathing problems.
- OHTUVAYRE is used to improve symptoms of COPD for better breathing and to reduce the number of flare-ups (the worsening of your COPD symptoms for several days).
- OHTUVAYRE is used long-term as 1 ampule of OHTUVAYRE, 2 times each day (1 in the morning and 1 in the evening) inhaled through your nebulizer that is fitted with a mouthpiece.
- OHTUVAYRE is not used to relieve sudden breathing problems and will not replace an inhaled rescue medicine.
- OHTUVAYRE should not be used in children. It is not known if OHTUVAYRE is safe and effective in children.

Do not use OHTUVAYRE if you have had an allergic reaction to ensifentrine or any of the ingredients in OHTUVAYRE. See "What are the ingredients in OHTUVAYRE?" at the end of this Patient Information leaflet for a complete list of ingredients in OHTUVAYRE.

Before taking OHTUVAYRE, tell your healthcare provider about all your medical conditions, including if you:

- have or have had a history of mental health problems including depression and suicidal behavior.
- have liver problems.
- are pregnant or plan to become pregnant. It is not known if OHTUVAYRE may harm your unborn baby.
- are breastfeeding. It is not known if the medicine in OHTUVAYRE passes into your breast milk and if it can harm your baby.

Tell your healthcare provider about all the medicines you take, including prescription and over-the-counter medicines, vitamins, and herbal supplements.

How should I use OHTUVAYRE?
Read the step-by-step instructions for using OHTUVAYRE at the end of this Patient Information leaflet.

- OHTUVAYRE is only for use with a nebulizer.
- Do not use OHTUVAYRE unless your healthcare provider has taught you how to use it with your nebulizer and you understand how to use it correctly.
- Use OHTUVAYRE exactly as your healthcare provider tells you to use it. Do not use OHTUVAYRE more often than prescribed.
- OHTUVAYRE is taken as a breathing treatment by oral (mouth) inhalation and should be used with a standard jet nebulizer with a mouthpiece connected to an air compressor.
- Do not mix other medicines with OHTUVAYRE in your nebulizer.
- Shake the OHTUVAYRE ampule vigorously immediately before using it. When shaken, OHTUVAYRE will appear cloudy and yellow to pale yellow in color.
- Use 1 ampule of OHTUVAYRE 2 times a day, 1 time in the morning and 1 time in the evening. Do not use more than 1 ampule of OHTUVAYRE in a single treatment. Do not use more than 2 ampules of OHTUVAYRE a day.
- If you use too much OHTUVAYRE, call your healthcare provider or go to the nearest hospital emergency room right away if you have any unusual symptoms, such as increased heart rate or headaches.
- OHTUVAYRE does not relieve sudden symptoms of COPD and you should not use extra doses of OHTUVAYRE to relieve these sudden symptoms. Always have an inhaled rescue medicine with you to treat sudden symptoms. If you do not have an inhaled rescue medicine, call your healthcare provider to have one prescribed for you.
- Call your healthcare provider or get emergency medical care right away if:
  - your breathing problems get worse.
  - you need to use your inhaled rescue medicine more often than usual.
  - your inhaled rescue medicine does not relieve your symptoms.
- Do not stop using OHTUVAYRE, even if you are feeling better, unless your healthcare provider tells you to, because your symptoms might get worse.
- Throw away the OHTUVAYRE ampules immediately after use. Due to their small size, the ampules pose a danger of choking to young children.

What are the possible side effects of OHTUVAYRE?
OHTUVAYRE can cause serious side effects, including:

- Sudden breathing problems immediately after inhaling your medicine. If you have sudden breathing problems immediately after inhaling your medicine, stop using OHTUVAYRE and call your healthcare provider right away or go to the nearest hospital emergency room right away.
- Mental health problems including suicidal thoughts and behavior. You may experience mood or behavior changes when taking OHTUVAYRE. Call your healthcare provider right away if you have any of these symptoms, especially if they are new, worse, or worry you:

- thoughts of suicide or dying
- attempt to commit suicide
- trouble sleeping (insomnia)

- new or worse anxiety
- new or worse depression
- acting on dangerous impulses
- other unusual changes in your behavior or mood

Most common side effects of OHTUVAYRE include:

- back pain
- high blood pressure
- bladder infection
- diarrhea

These are not all the possible side effects of OHTUVAYRE.
Call your doctor for medical advice about side effects. You may report side effects to FDA at 1-800-FDA-1088.

How should I store OHTUVAYRE?

- Store OHTUVAYRE at room temperature between 68°F to 77°F (20°C to 25°C). Keep OHTUVAYRE away from direct sunlight and excessive heat. Do not freeze.
- Store OHTUVAYRE in the unopened protective foil pouch and only open the foil pouch immediately before using OHTUVAYRE. For pouches of 5 ampules, remove one ampule and place the remaining ampules back into the pouch until next use.
- Throw away the used ampule and any leftover medicine after use.
- Do not use OHTUVAYRE after the expiration date provided on the foil pouch and ampule.
- Keep OHTUVAYRE and all medicines out of the reach of children.

General information about the safe and effective use of OHTUVAYRE.
Medicines are sometimes prescribed for purposes other than those listed in a Patient Information leaflet. Do not use OHTUVAYRE for a condition for which it was not prescribed. Do not give OHTUVAYRE to other people, even if they have the same symptoms that you have. It may harm them.
You can ask your healthcare provider or pharmacist for information about OHTUVAYRE that is written for health professionals.

What are the ingredients in OHTUVAYRE?
Active ingredient: ensifentrine
Inactive ingredients: dibasic sodium phosphate, monobasic sodium phosphate, polysorbate 20, sodium chloride, sorbitan monolaurate and water for injection.
Manufactured for:
Verona Pharma, Inc.
Raleigh, NC, 27615
©2025. Verona Pharma plc and its affiliates
Verona Pharma, OHTUVAYRE and the Verona Pharma and OHTUVAYRE logos are all trademarks of Verona Pharma plc

This Patient Information has been approved by the U.S. Food and Drug Administration. Approved: 07/2025
PIL002

INSTRUCTIONS FOR USE
OHTUVAYRE (OH-too-vare)
(ensifentrine)
inhalation suspension, for oral inhalation

This Instructions for Use contains information on how to use OHTUVAYRE.

To use OHTUVAYRE, you will also need a jet nebulizer machine and air compressor.

OHTUVAYRE
single-dose ampule

Important Information You Need to Know Before Using OHTUVAYRE

- For oral inhalation only
- OHTUVAYRE is used only in a standard jet nebulizer machine with a mouthpiece connected to an air compressor.
- Do not mix other medicines with OHTUVAYRE in your nebulizer.
- OHTUVAYRE comes in an ampule that is sealed in a foil pouch. Do not open the sealed pouch until you are ready to use a dose of OHTUVAYRE.
- Use your OHTUVAYRE right away after opening. For pouches of 5 ampules, place the remaining ampules back into the pouch until next use.
- Throw away the OHTUVAYRE ampules immediately after use. Due to their small size, the ampules pose a danger of choking to young children.

Preparing to Use OHTUVAYRE

- Make sure you know how to use your nebulizer machine before you use it to breathe in OHTUVAYRE.
- Read the following steps before using OHTUVAYRE. If you have any questions, ask your healthcare provider or pharmacist.

Using OHTUVAYRE

Step 1. Open Pouch: Open the foil pouch by tearing along the seam of the pouch. Remove an ampule of OHTUVAYRE from the foil pouch. For pouches of 5 ampules, remove one ampule and place the remaining ampules back into the pouch until next use.

Step 2. Shake Ampule: Shake ampule vigorously until the contents are thoroughly mixed (see Figure A). The contents will appear cloudy and yellow to pale yellow in color.

Figure A

Step 3. Open Ampule: Carefully twist open the top of the ampule and use the contents right away (see Figure B).

Figure B

Step 4. Add Medicine: Squeeze all the medicine from the ampule into the nebulizer cup (reservoir) (see Figure C).

Figure C

Step 5. Attach Mouthpiece: If a separate mouthpiece attachment is supplied with your nebulizer, connect the mouthpiece to the nebulizer (see Figure D).

Figure D

Step 6. Connect the Nebulizer to the Compressor: Firmly insert one end of the tubing to the compressor. Insert the other end of the tubing to the bottom of the nebulizer cup (reservoir) (see Figure E).

Figure E

Step 7. Prepare for Treatment: Sit in a comfortable, upright position. Place the mouthpiece in your mouth and close your lips around the mouthpiece (see Figure F).

Figure F

Step 8. Begin Treatment: Turn on the compressor to begin treatment.

Step 9. Breathe in Medicine: Breathe calmly, deeply, and evenly as possible until no more mist is seen in the nebulizer reservoir. Your treatment will typically take about 5 to 7 minutes. When you no longer see any mist in the nebulizer, your treatment is completed. Turn the compressor off.

Storing OHTUVAYRE and Nebulizer

- Clean and store your nebulizer. See the manufacturer's instructions that come with your nebulizer for how to clean and store your nebulizer.
- Store OHTUVAYRE ampules in the protective foil pouch in the carton at room temperature between 68°F to 77°F (20°C to 25°C) away from direct sunlight and excessive heat, in an upright position as indicated on the carton. Do not freeze.

Additional Information

Please call Verona Pharma at 1-888-672-0371 for more product information or to report problems with the product. Please call Verona Pharma at 1-888-672-0371 or FDA at 1-800-FDA-1088 or www.fda.gov/medwatch to report adverse reactions.

Manufactured for: Verona Pharma, Inc., Raleigh, NC 27615

©2025. Verona Pharma plc and its affiliates

Verona Pharma, OHTUVAYRE and the Verona Pharma and OHTUVAYRE logos are all trademarks of Verona Pharma plc

This Instructions for Use has been approved by the U.S. Food and Drug Administration.
Approved: 7/2025

IFU002

PRINCIPAL DISPLAY PANEL - 3 mg/2.5 mL Ampule Carton

Ohtuvayre™

(ensifentrine)
Inhalation Suspension

3 mg/2.5 mL

FOR ORAL INHALATION ONLY

↑ STORE UPRIGHT

NDC: 83034-003-60

Rx Only
60 UNIT-DOSE AMPULES